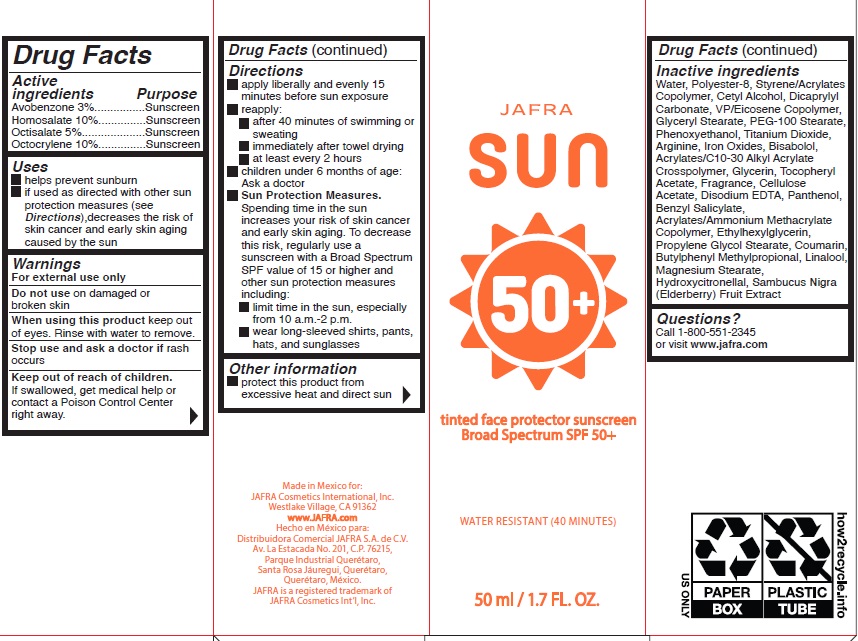 DRUG LABEL: Jafra Sun tinted face protector sunscreen broad spectrum 50
NDC: 68828-293 | Form: CREAM
Manufacturer: Distribuidora Comercial Jafra, S.A. de C.V.
Category: otc | Type: HUMAN OTC DRUG LABEL
Date: 20251021

ACTIVE INGREDIENTS: AVOBENZONE 3 g/100 mL; OCTOCRYLENE 10 g/100 mL; HOMOSALATE 10 g/100 mL; OCTISALATE 5 g/100 mL
INACTIVE INGREDIENTS: GLYCERYL MONOSTEARATE; POLYESTER-8 (1400 MW, CYANODIPHENYLPROPENOYL CAPPED); EUROPEAN ELDERBERRY; FERRIC OXIDE RED; PEG-100 STEARATE; MAGNESIUM STEARATE; CELLULOSE ACETATE; CETYL ALCOHOL; .ALPHA.-TOCOPHEROL ACETATE; VINYLPYRROLIDONE/EICOSENE COPOLYMER; WATER; EDETATE DISODIUM; GLYCERIN; FERRIC OXIDE YELLOW; CARBOMER COPOLYMER TYPE B (ALLYL PENTAERYTHRITOL CROSSLINKED); PANTHENOL; PHENOXYETHANOL; DICAPRYLYL CARBONATE; PROPYLENE GLYCOL MONOSTEARATE; TITANIUM DIOXIDE; ARGININE; LEVOMENOL; ETHYLHEXYLGLYCERIN; BENZYL SALICYLATE; COUMARIN; BUTYLPHENYL METHYLPROPIONAL; LINALOOL, (+/-)-; HYDROXYCITRONELLAL; FERROSOFERRIC OXIDE

Jafra Sun tinted face protector sunscreen broad spectrum 50+

Active Ingredients Purpose

Avobenzone 3%..............Sunscreen

Homosalate 10%.............Sunscreen

Octisalate 5%..................Sunscreen

Octocrylene 10%.............Sunscreen

Uses

- helps prevent sunburn
- if used as directed with other sun protection measures (see Directions), decreases the risk of skin cancer and early skin aging caused by the sun

Warnings

- For external use only
- Do not use on damaged or broken skin
- When using this product keep out of eyes. Rinse with water to remove.
- Stop use and ask a doctor ifrash occurs.
- Keep out of reach of children. If swallowed, get medical help or contact a Poison Control Center right away.

Directions

- Apply liberally and evenly 15 minutes before sun exposure
- reapply:

• after 40 minutes of swimming or sweating
• immediately after towel drying
• at least every 2 hours

- Children under 6 months of age: Ask a doctor
- Sun Protection Measures.Spending time in the sun increases your risk of skin cancer and early skin aging. To decrease this risk, regularly use a sunscreen with a Broad Spectrum SPF value of 15 or higher and other sun protection measures including:

• limit time in the sun, especially from 10 a.m. - 2 p.m.
• wear long-sleeved shirts, pants, hats, and sunglasses

Other information

protect this product from excessive heat and direct sun

Inactive Ingredients

Water, Polyester-8, Styrene/Acrylates Copolymer, Cetyl Alcohol, Dicaprylyl Carbonate, VP/Eicosene Copolymer, Glyceryl Stearate, PEG-100 Stearate, Phenoxyethanol, Titanium Dioxide, Arginine, Iron Oxides, Bisabolol, Acrylates/C10-30 Alkyl Acrylate Crosspolymer, Glycerin, Tocopheryl Acetate, Fragrance, Cellulose Acetate, Disodium EDTA, Panthenol, Benzyl Salicylate, Acrylates /Ammonium Methacrylate Copolymer, Ethylhexylglycerin, Propylene Glycol Stearate, Coumarin, Butylphenyl Methylpropional, Linalool, Magnesium Stearate, Hydroxycitronellal, Sambucus Nigra (Elderberry) Fruit Extract

Questions?Call 1-800-551-2345 or visit www .jafra.com